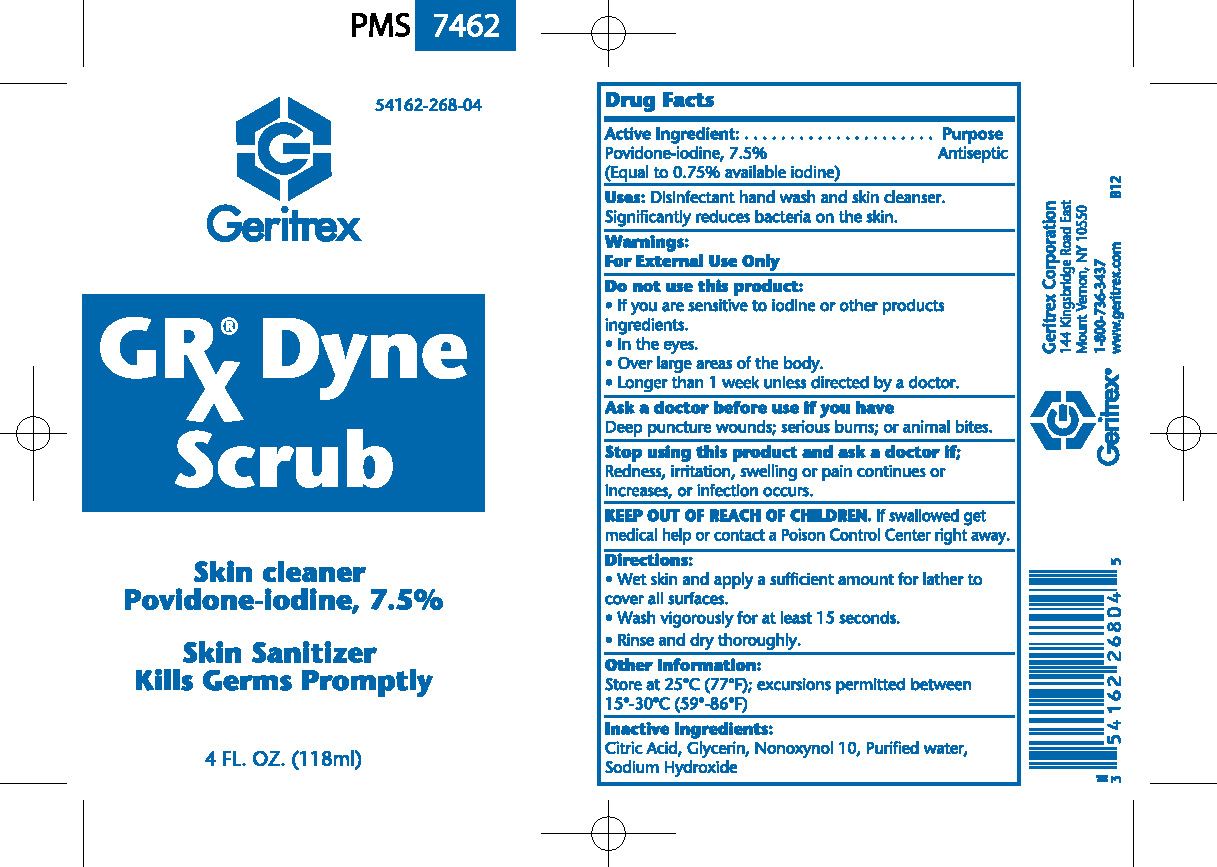 DRUG LABEL: GRx Dyne Scrub
NDC: 54162-268 | Form: SOLUTION
Manufacturer: Geritrex Corp.
Category: otc | Type: HUMAN OTC DRUG LABEL
Date: 20120703

ACTIVE INGREDIENTS: POVIDONE-IODINE 7500 mg/100 mL
INACTIVE INGREDIENTS: CITRIC ACID MONOHYDRATE; GLYCERIN; NONOXYNOL-10; WATER; SODIUM HYDROXIDE

GRx Dyne Scrub

Active Ingredient

Active Ingredient: Purpose
Povidone-Iodine, 7.5% Antiseptic
(Equal to 0.75% available Iodine)

uses

Disinfectant hand wash and skin cleanser.

Significantly reduces bacteria on the skin.

Directions

Wet skin and apply a sufficient amount for lather to

cover all surfaces.

Wash vigorously for at least 15 seconds.

Rinse and dry thoroughly.

DOSAGE AND ADMINISTRATION

Wash vigorously for at least 15 seconds.

Warnings

For External Use Only

Do not use this product:

If you are sensitive to iodine or other products ingredients.

In the eyes.

Over large areas of the body.

Longer than 1 week unless directed by a doctor.

Ask a doctor before use if you have

Deep puncture wounds: serious burns: or animal bites.

Stop using this product and ask a doctor if;

Redness, irritation, swelling, or pain continues or increases, or infection occurs.

Inactive Ingredient

Citric acid, glycerin, Nonoxynol 10, purified water, sodium hydroxide

STORAGE AND HANDLING

Store at 25'C (77'F); excursions permitted between

15'-30'C (59'-86'F)

KEEP OUT OF REACH OF CHILDREN

If swallowed get medical help or contact a Poison Control Center right away.

PACKAGE LABEL

Enter section text here